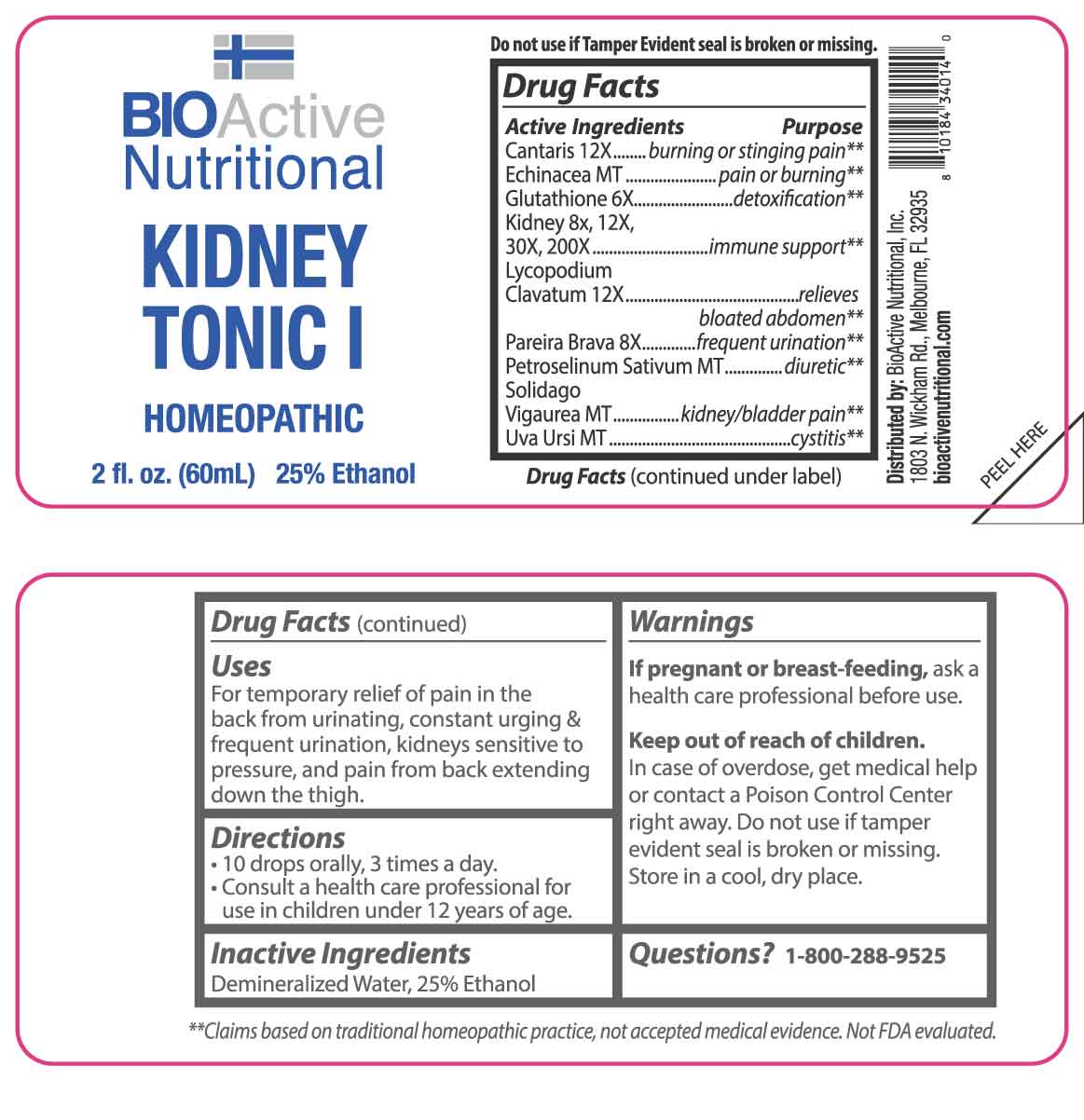 DRUG LABEL: Kidney Tonic
NDC: 43857-0559 | Form: LIQUID
Manufacturer: BioActive Nutritional, Inc.
Category: homeopathic | Type: HUMAN OTC DRUG LABEL
Date: 20250404

ACTIVE INGREDIENTS: ECHINACEA ANGUSTIFOLIA WHOLE 1 [hp_X]/1 mL; PETROSELINUM CRISPUM WHOLE 1 [hp_X]/1 mL; SOLIDAGO VIRGAUREA FLOWERING TOP 1 [hp_X]/1 mL; ARCTOSTAPHYLOS UVA-URSI LEAF 1 [hp_X]/1 mL; GLUTATHIONE 6 [hp_X]/1 mL; CHONDRODENDRON TOMENTOSUM ROOT 8 [hp_X]/1 mL; PORK KIDNEY 8 [hp_X]/1 mL; LYTTA VESICATORIA 12 [hp_X]/1 mL; LYCOPODIUM CLAVATUM SPORE 12 [hp_X]/1 mL
INACTIVE INGREDIENTS: WATER; ALCOHOL

DRUG FACTS:

ACTIVE INGREDIENTS:

Cantharis 12X, Echinacea MT, Glutathione 6X, Kidney 8X, 12X, 30X, 200X, Lycopodium Clavatum 12X, Pareira Brava 8X, Petroselinum Sativum MT, Solidago Virgaurea MT, Uva-Ursi MT.

PURPOSE:

Cantharis – burning or stinging pain,** Echinacea – pain or burning,** Glutathione - detoxification,** Kidney – immune support,** Lycopodium Clavatum – relieves bloated abdomen,** Pareira Brava – frequent urination,** Petroselinum Sativum - diuretic,** Solidago Virgaurea – kidney/bladder pain,** Uva-Ursi – cystitis**
**Claims based on traditional homeopathic practice, not accepted medical evidence. Not FDA Evaluated.

USES:

For temporary relief of pain in the back from urinating, constant urging & frequent urination, kidneys sensitive to pressure, and pain from back extending down the thigh.

WARNINGS:

If pregnant or breast-feeding, ask a health care professional before use.

Keep out of reach of children. In case of overdose, get medical help or contact a Poison Control Center right away.

Do not use if tamper evident seal is broken or missing.

Store in a cool, dry place.

KEEP OUT OF REACH OF CHILDREN:

In case of overdose, get medical help or contact a Poison Control Center right away.

DIRECTIONS:

• 10 drops orally, 3 times a day.

• Consult a health care professional for use in children under 12 years of age.

INACTIVE INGREDIENTS:

Demineralized Water, 25% Ethanol

QUESTIONS:

Distributed by:
BioActive Nutritional, Inc.
1803 N. Wickham Rd.
Melbourne, FL 32935
bioactivenutritional.com

1-800-288-9525

PACKAGE LABEL DISPLAY:

BIOActive Nutritional

KIDNEY TONIC I

HOMEOPATHIC

2 FL OZ (60 ml)